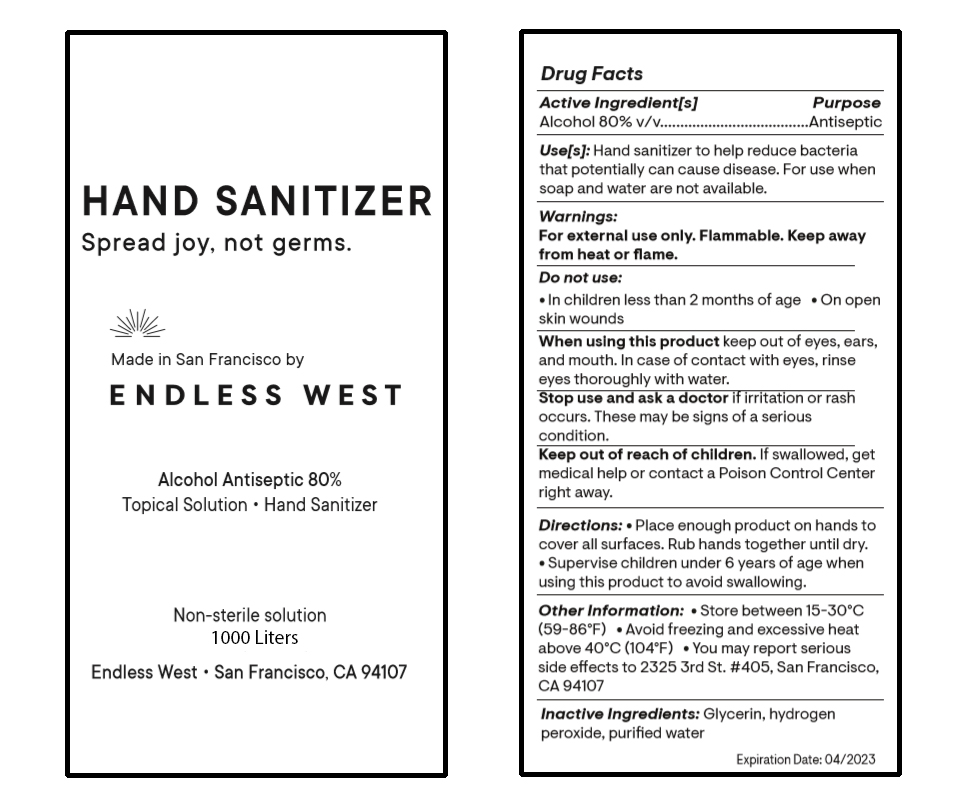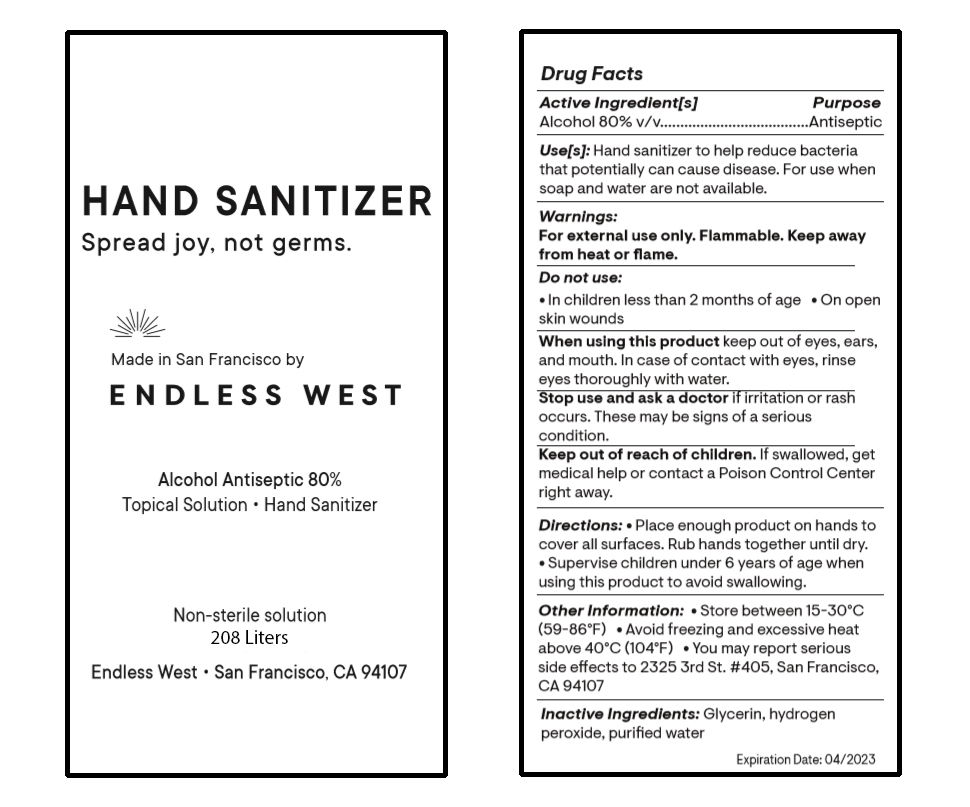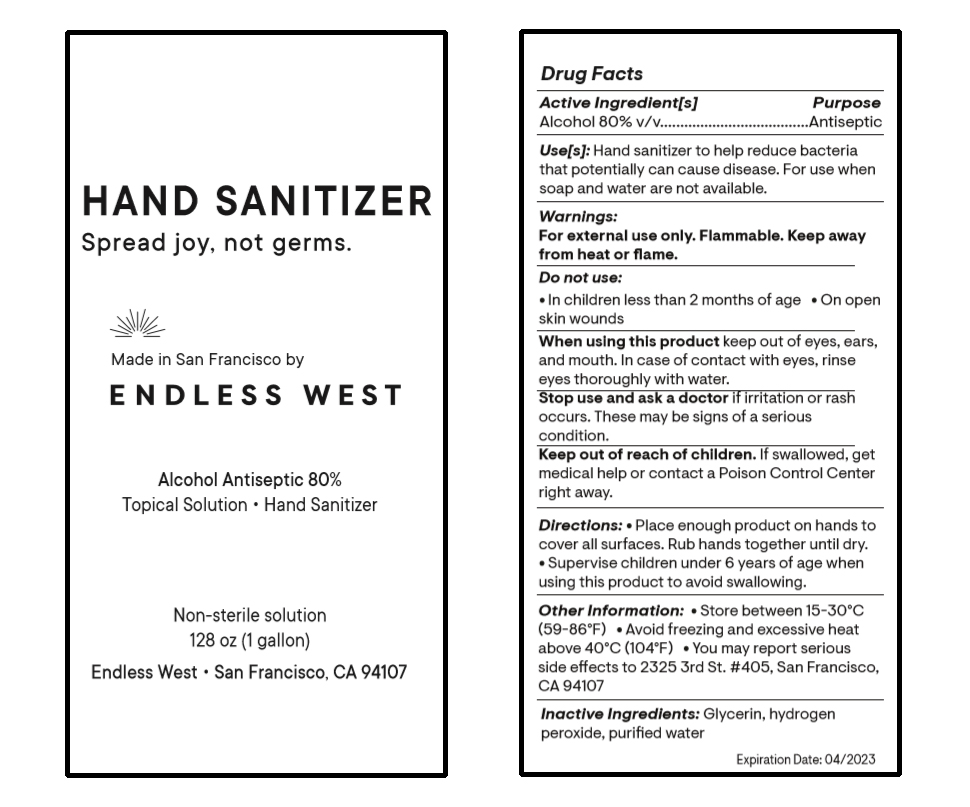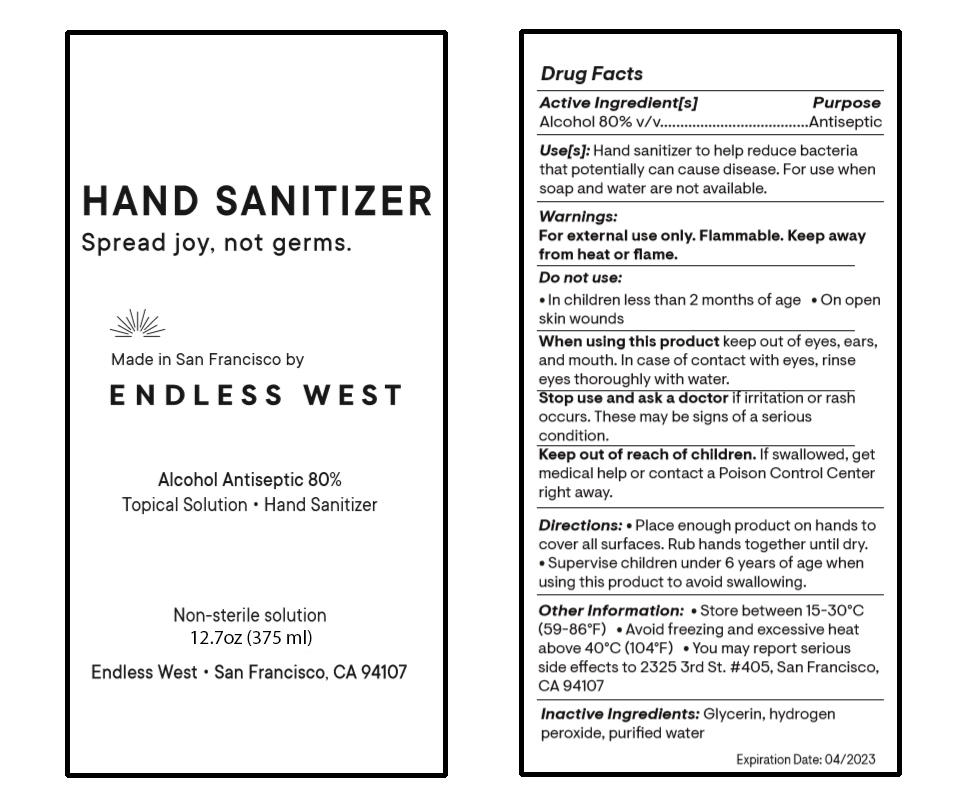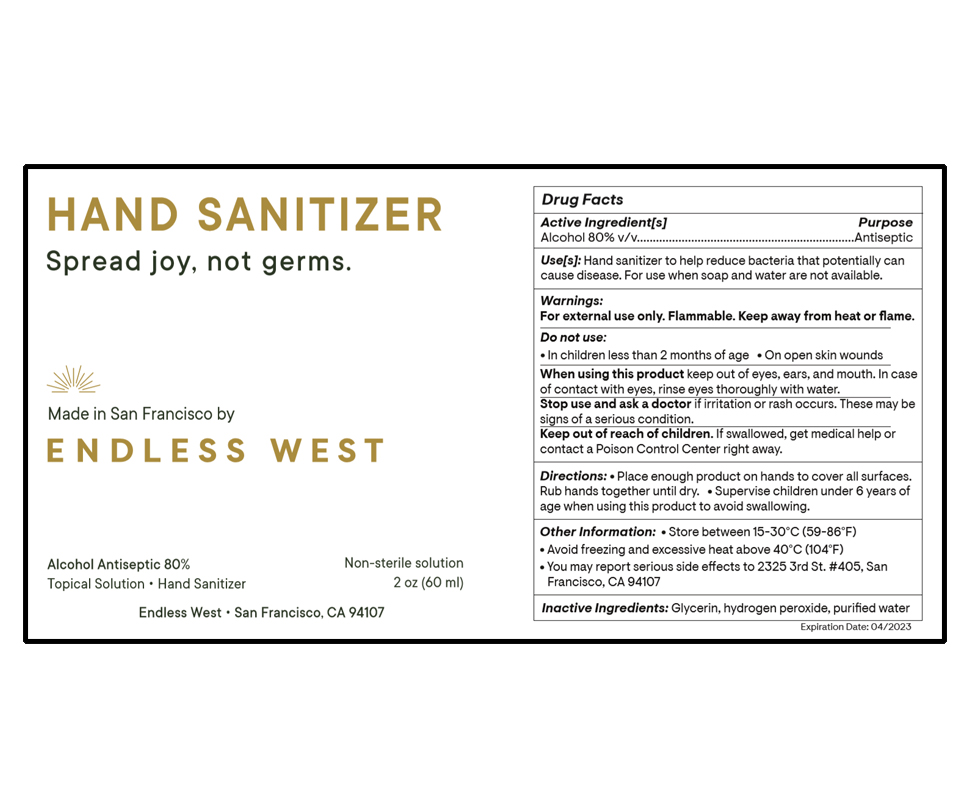 DRUG LABEL: Hand Sanitizer
NDC: 74065-001 | Form: SOLUTION
Manufacturer: Ava Food Labs, Inc.
Category: otc | Type: HUMAN OTC DRUG LABEL
Date: 20200330

ACTIVE INGREDIENTS: ALCOHOL 80 mL/100 mL
INACTIVE INGREDIENTS: GLYCERIN 1.45 mL/100 mL; HYDROGEN PEROXIDE 0.125 mL/100 mL; WATER

Hand Sanitizer by Ava Food Labs, Inc. dba Endless West

Active Ingredient(s)

Alcohol 80% v/v. Purpose: Antiseptic

Purpose

Antiseptic, Hand Sanitizer

Use

Hand Sanitizer to help reduce bacteria that potentially can cause disease. For use when soap and water are not available.

Warnings

For external use only. Flammable. Keep away from heat or flame

Do not use

- in children less than 2 months of age
- on open skin wounds

When using this product keep out of eyes, ears, and mouth. In case of contact with eyes, rinse eyes thoroughly with water.
Stop use and ask a doctor if irritation or rash occurs. These may be signs of a serious condition.
Keep out of reach of children. If swallowed, get medical help or contact a Poison Control Center right away.

Stop use and ask a doctor if irritation or rash occurs. These may be signs of a serious condition.

Keep out of reach of children. If swallowed, get medical help or contact a Poison Control Center right away.

Directions

- Place enough product on hands to cover all surfaces. Rub hands together until dry.
- Supervise children under 6 years of age when using this product to avoid swallowing.

Other information

- Store between 15-30C (59-86F)
- Avoid freezing and excessive heat above 40C (104F)
- You may report serious side effects to 2325 3rd St. #405, San Francisco, CA 94107

Inactive ingredients

glycerin, hydrogen peroxide, purified water

Package Label - Principal Display Panel

60 mL NDC: 74065-001-01

3785 mL NDC: 74065-001-02

3785 mL NDC: 74065-001-03

208000 mL NDC: 74065-001-04

1000000 mL NDC: 74065-001-05

60 mL NDC: 74065-001-06

375 mL NDC: 74065-001-07